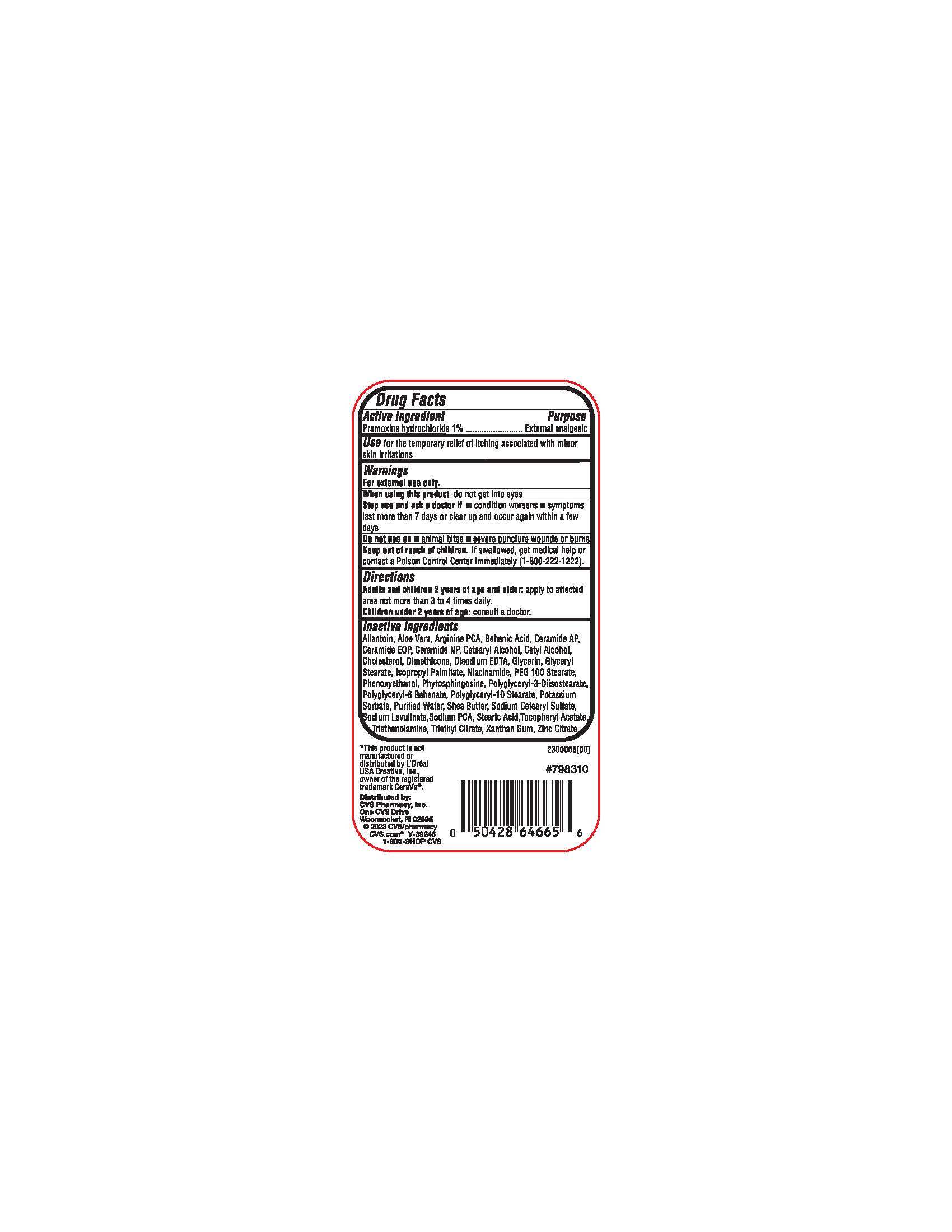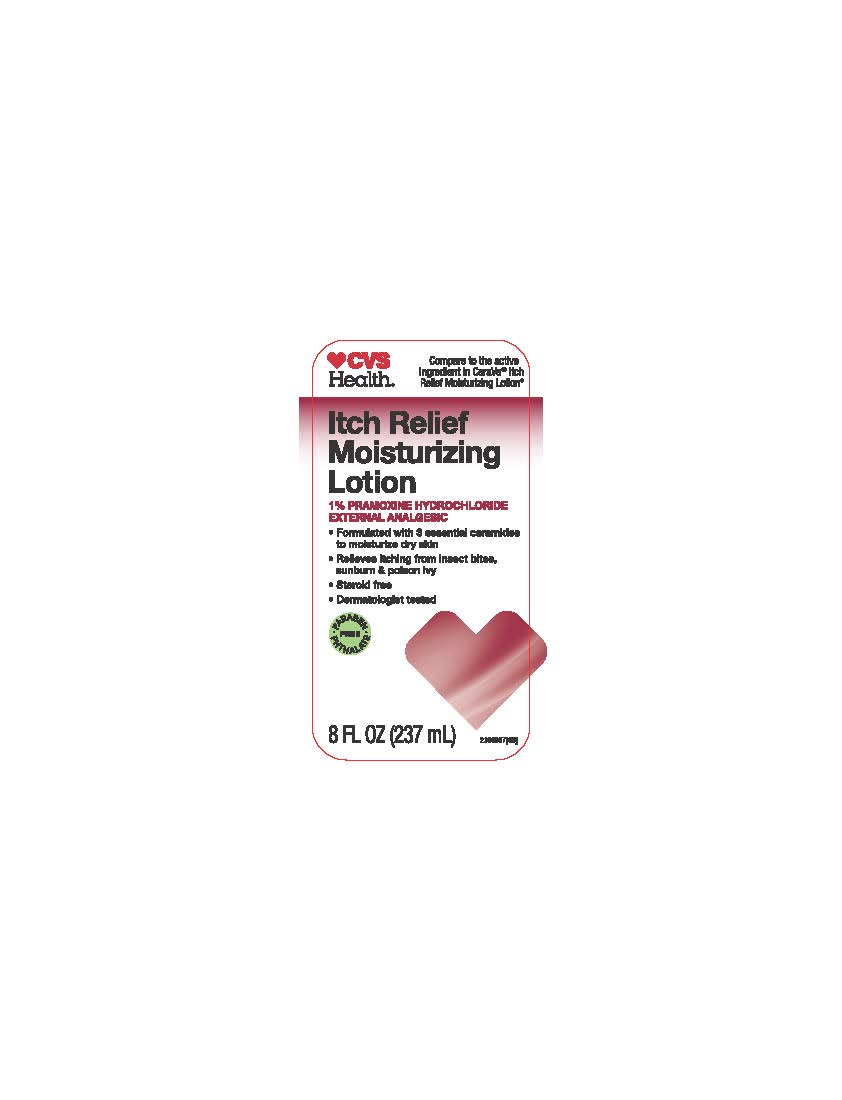 DRUG LABEL: CVS Itch relief moisturizing
NDC: 51316-144 | Form: LOTION
Manufacturer: CVS Health
Category: otc | Type: HUMAN OTC DRUG LABEL
Date: 20231018

ACTIVE INGREDIENTS: PRAMOXINE HYDROCHLORIDE 1 g/100 mL
INACTIVE INGREDIENTS: PHENOXYETHANOL; CERAMIDE AP; ISOPROPYL PALMITATE; CETOSTEARYL ALCOHOL; POLYGLYCERYL-3 DISTEARATE; TROLAMINE; SODIUM PYRROLIDONE CARBOXYLATE; ALPHA-TOCOPHEROL ACETATE; XANTHAN GUM; ALOE VERA LEAF; CERAMIDE NP; WATER; SHEA BUTTER; PEG-100 STEARATE; GLYCERYL MONOSTEARATE; STEARIC ACID; NIACINAMIDE; ZINC CITRATE; DIMETHICONE; EDETATE DISODIUM; GLYCERIN; CETYL ALCOHOL; ALLANTOIN; ARGININE; CERAMIDE 1

CVS Itch relief moisturizing Lotion

ACTIVE INGREDIENT

Pramoxine Hydrochloride 1%

PURPOSE

External analgesic

INDICATIONS AND USAGE

Use for the temporary relief of itching associated with minor skin irritations

WARNINGS

For external use only

WHEN USING

do not get into eyes

Stop use and ask a doctor if

condition worsens

symptoms last more than 7 days or clear up and occur again within a few days

Do not use on

- animal bites
- severe puncture wounds or burns

KEEP OUT OF REACH OF CHILDREN

If swallowed, get medical help or contact a Poison Control Immediately (1-800-222-1222)

DOSAGE AND ADMINISTRATION

Adults and Children 2 years of age and older: apply to affected area not more than 3 to 4 times daily

Children under 2 years of age: Consult a doctor

INACTIVE INGREDIENT

Allantion, Aloe Vera, Arginine PCA, Behenic Acid, Ceramide AP, Ceramide EOP, Ceramide NP, Cetearyl Alcohol, Cetyl Alcohol, Cholesterol, Dimethicone, Disodium EDTA, Glycerin, Glyceryl Stearate, Isopropyl Palmitate, Niacinamide, PEG 100 Stearate, Isopropyl Palmitate, Niacinamide, PEG 100 Stearate, Phenoxyethanol, Phytosphingosine, Polyglyceryl-2- Diisostearate, polyglyceryl-6 Behenate, Polyglyceryl-10 Stearate, Potassium Sorbate, Purified water, Shea Butter, Sodium Cetearyl Sulfate, Sodium Levulinate, Sodium PCA, Stearic Acid, Tocopheryl Acetate, Triethanolamine, Triethyl Citrate, Xanthan Gum, Zinc Citrate.